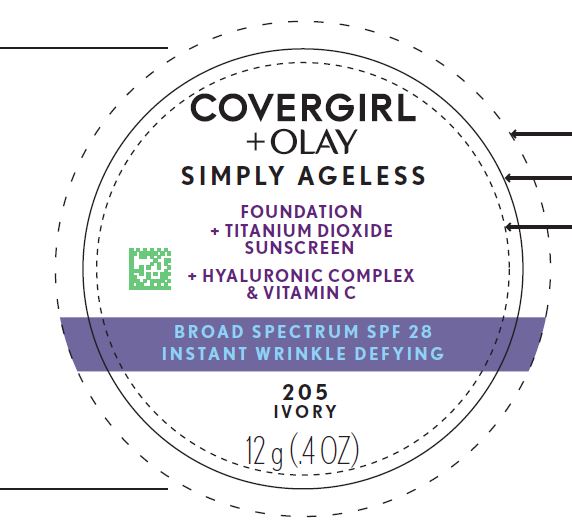 DRUG LABEL: Covergirl plus Olay Simply Ageless
NDC: 22700-155 | Form: CREAM
Manufacturer: Noxell Corporation
Category: otc | Type: HUMAN OTC DRUG LABEL
Date: 20241119

ACTIVE INGREDIENTS: TITANIUM DIOXIDE 4.9 mg/0.1 g
INACTIVE INGREDIENTS: WATER; CYCLOMETHICONE 5; TALC; BUTYLENE GLYCOL; NIACINAMIDE; CANDELILLA WAX; ISOTRIDECYL ISONONANOATE; CERESIN; N-ACETYLGLUCOSAMINE; SILICON DIOXIDE; PEG-9 POLYDIMETHYLSILOXYETHYL DIMETHICONE; SORBITAN ISOSTEARATE; .ALPHA.-TOCOPHEROL ACETATE; DIMETHICONE; PANTHENOL; EDETATE DISODIUM; DISODIUM STEAROYL GLUTAMATE; STEARIC ACID; ALUMINUM HYDROXIDE; PHENOXYETHANOL; IODOPROPYNYL BUTYLCARBAMATE; FERRIC OXIDE RED

Covergirl plus Olay Simply Ageless
Foundation plus Titanium Dioxide Sunscreen Broad Spectrum SPF 28 (All shades)

Drug Facts

Active ingredient

Titanium Dioxide 4.9%

Purpose

Sunscreen

Uses

- helps prevent sunburn
- if used as directed with other sun protection measures (see Directions), decreases the risk of skin cancer and early skin aging caused by the sun.

Warnings

- For external use only

- Do not use on damaged or broken skin

- When using this product keep out of eyes. Rinse with water to remove.

- Stop use and ask a doctor if rash occurs.

- Keep out of reach of children. If product is swallowed, get medical help or contact a Poison Control Center right away.

Directions

- apply liberally 15 minutes before sun exposure
- reapply at least every 2 hours
- use water resistant sunscreen if swimming or sweating.
- Sun Protection Measures. Spending time in the sun increases your risk of skin cancer and early skin aging. To decrease this risk, regularly use a sunscreen with a Broad Spectrum SPF value of 15 or higher and other sun protection measures including:
  - limit time in sun, especially from 10 a.m. – 2 p.m
  - wear long-sleeved shirts, pants, hats, and sunglasses
- children under 6 months: ask a doctor.

Other information

Protect this product from excessive heat and direct sun

Inactive ingredients

Water, cyclopentasiloxane, talc, butylene glycol, niacinamide, euphorbia cerifera (candelilla) wax, isotridecyl isononanoate, ceresin, acetyl glucosamine, silica, peg-9 polydimethylsiloxyethyl dimethicone, sorbitan isostearate, tocopheryl acetate, dimethicone, methicone, panthenol, disodium edta, disodium stearoyl glutamate, stearic acid, hydrogen dimethicone, aluminum hydroxide, phenoxyethanol, hydroxypropyl cyclodextrin, iodopropynyl butylcarbamate.
MAY CONTAIN: Iron oxides, titanium dioxide.

Questions?

Call 1-800-426-8374

Principal Display Panel - 12 g (0.4 OZ) Jar Label

COVERGIRL

+OLAY

SIMPLY AGELESS

FOUNDATION

+ TITANIUM DIOXIDE

SUNSCREEN

+ HYALURONIC COMPLEX

& VITAMIN C

BROAD SPECTRUM SPF 28

INSTANT WRINKLE DEFYING

205IVORY

12 g (0.4 OZ)